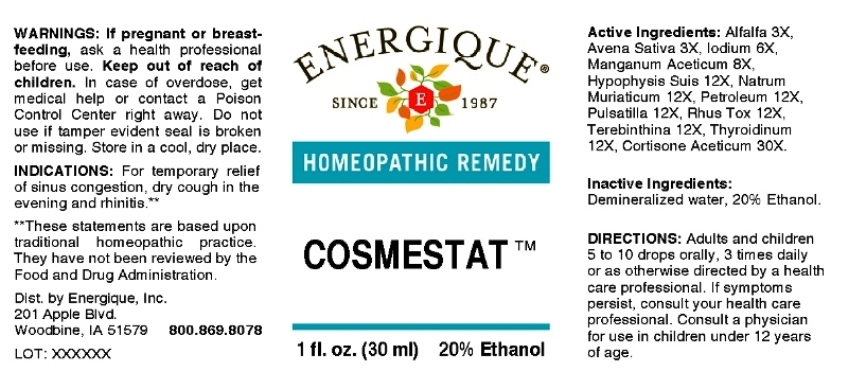 DRUG LABEL: Cosmestat
NDC: 44911-0671 | Form: LIQUID
Manufacturer: Energique, Inc.
Category: homeopathic | Type: HUMAN OTC DRUG LABEL
Date: 20230417

ACTIVE INGREDIENTS: MEDICAGO SATIVA WHOLE 3 [hp_X]/1 mL; AVENA SATIVA FLOWERING TOP 3 [hp_X]/1 mL; IODINE 6 [hp_X]/1 mL; LYCOPERDON UTRIFORME FRUITING BODY 12 [hp_X]/1 mL; FORMALDEHYDE SOLUTION 12 [hp_X]/1 mL; SUS SCROFA PITUITARY GLAND 12 [hp_X]/1 mL; MANGANESE ACETATE TETRAHYDRATE 12 [hp_X]/1 mL; SODIUM CHLORIDE 12 [hp_X]/1 mL; KEROSENE 12 [hp_X]/1 mL; PULSATILLA PRATENSIS WHOLE 12 [hp_X]/1 mL; TOXICODENDRON PUBESCENS LEAF 12 [hp_X]/1 mL; TURPENTINE OIL 12 [hp_X]/1 mL; THYROID, BOVINE 12 [hp_X]/1 mL; CORTISONE ACETATE 30 [hp_X]/1 mL
INACTIVE INGREDIENTS: WATER; ALCOHOL

DRUG FACTS:

ACTIVE INGREDIENTS:

(in each drop): 9.06% of Bovista 12X, Cortisone Aceticum 30X, Formalinum 12X, Hypophysis Suis 12X, Manganum Aceticum 12X, Natrum Muriaticum 12X, Petroleum 12X, Pulsatilla 12X, Rhus Tox 12X, Terebinthina 12X, Thyroidinum 12X; 0.10% of Alfalfa 3X, Avena Sativa 3X, Iodium 6X.

PURPOSE:

For temporary relief of sinus congestion, dry cough in the evening and rhinitis.**

**Claims based on traditional homeopathic practice, not medical evidence. Not FDA evaluated.

WARNINGS:

If pregnant or breastfeeding, ask a health professional before use.

Keep out of reach of children. In case of overdose, get medical help or contact a Poison Control Center right away.

Do not use if tamper evident seal is broken or missing.

Store in a cool, dry place.

KEEP OUT OF REACH OF CHILDREN:

In case of overdose, get medical help or contact a Poison Control Center right away.

DIRECTIONS:

Adults and children 5 to 10 drops orally, 3 times daily or as otherwise directed by a health care professional. If symptoms persist for more than 7 days, consult your health care professional. Consult a physician for use in children under 12 years of age.

INDICATIONS:

For temporary relief of sinus congestion, dry cough in the evening and rhinitis.**

**Claims based on traditional homeopathic practice, not medical evidence. Not FDA evaluated.

INACTIVE INGREDIENTS:

Demineralized water, 20% Ethanol.

QUESTIONS:

Dist. by Energique, Inc.
201 Apple Blvd.
Woodbine, IA 51579 800.869.8078

PACKAGE LABEL DISPLAY:

ENERGIQUE

SINCE 1987

HOMEOPATHIC REMEDY

COSMESTAT

1 fl. oz. (30 ml)